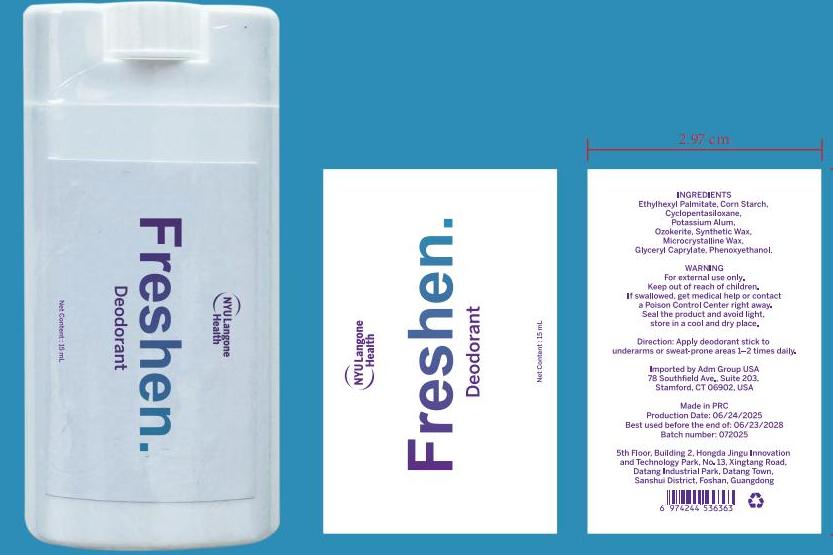 DRUG LABEL: NYU Langone Health  Deodorant
NDC: 83566-559 | Form: OINTMENT
Manufacturer: Guangdong Aimu Biological Technology Co., Ltd
Category: otc | Type: HUMAN OTC DRUG LABEL
Date: 20250915

ACTIVE INGREDIENTS: ALUMINUM CHLOROHYDRATE 15 g/100 mL
INACTIVE INGREDIENTS: GLYCERYL CAPRYLATE; CYCLOHEXASILOXANE; STARCH, CORN; MICROCRYSTALLINE WAX; PHENOXYETHANOL; SYNTHETIC WAX (1200 MW); ETHYLHEXYL PALMITATE; CERESIN

Active ingredients

POTASSIUM ALUM 15%

Inactive ingredients

ETHYLHEXYL PALMITATE 26.6%
GLYCERYL CAPRYLATE 20%
CYCLOHEXASILOXANE 15%
OZOKERITE 10%
CORN STARCH 5%
SYNTHETIC WAX 5%
MICROCRYSTALLINE WAX 3%
PHENOXYETHANOL 0.4%

Purpose

remove ordor

Uses

Step1:Before using the deodorant, clean the armpit area with clean water or body wash to ensure the skin is clean

Step2:Apply the deodorant directly under the armpits and evenly cover the skin surface.

Step3:After applying, wait for a few minutes to allow the deodorizing stick to dry completely to ensure that its active ingredients can take effect.

Warnings

For external use only.

Stop Use

Stop use and ask doctor if rash occurs.

Do not use on damaged or broken skin.

When Using

When using this product keep out of eyes. Rinse with wate to remove.

Keep out of reach of children. lf swallowed, getmedical help or contact
Poison Control Center right away.

Dosage & administration

Squeeze out an appropriate amount of deodorant and spread